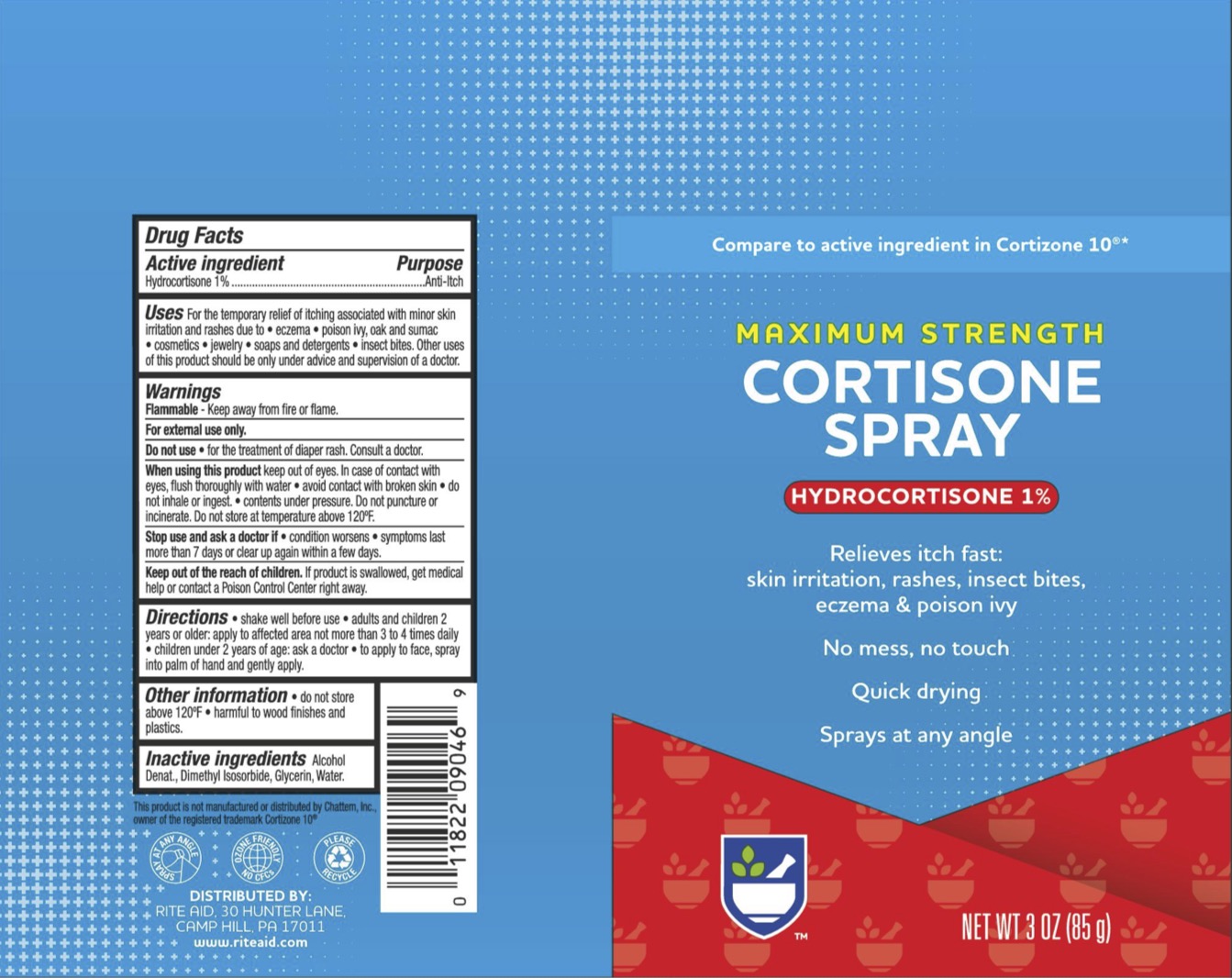 DRUG LABEL: Rite Aid Cortisone
NDC: 11822-0113 | Form: SPRAY
Manufacturer: Rite Aid
Category: otc | Type: HUMAN OTC DRUG LABEL
Date: 20241215

ACTIVE INGREDIENTS: HYDROCORTISONE 1 g/100 g
INACTIVE INGREDIENTS: ALCOHOL; DIMETHYL ISOSORBIDE; GLYCERIN; WATER

Rite Aid Cortison Spray, Hydrocortisone 1%

ACTIVE INGREDIENT

Hydrocortisone 1%

PURPOSE

Anti-itch

INDICATIONS AND USAGE

For the temporary relief of itching associated with minor skin irritation and rashes due to eczema, poison ivy, oak, and sumac, cosmetics, jewelry, soaps and detergents, and insect bites. Other uses of this product should be only under the advice and supervision of a doctor.

WARNINGS

For external use only. Flammable--Keep away from fire or flame. Do not use for the treatment of diaper rash. Consult a doctor. When using this product avoid contact with eyes. In case of contact with eyes, flush thoroughly with water, do not apply to wounds or damaged skin, and do not bandage tightly, do not use with a heating pad. Contents under pressure. Do not puncture or incinerate. Do not store at temperature above 120F. . Stop use and ask a doctor if condition worsens, if symptoms persist for more than 7 days or clear up and occur again within a few days.

KEEP OUT OF REACH OF CHILDREN

If swallowed, get medical help or contact a Poison Control Center right away.

DOSAGE AND ADMINISTRATION

Shake well before use. Adults and children 12 years of age and older, apply to the affected area not more than 3 to 4 times daily. Children under 12 years of age: ask a doctor. To apply to face, spray into palm of hand and gently apply.

INACTIVE INGREDIENT

Alcohol Denat., Dimethyl Isosorbide, Glycerin, Water